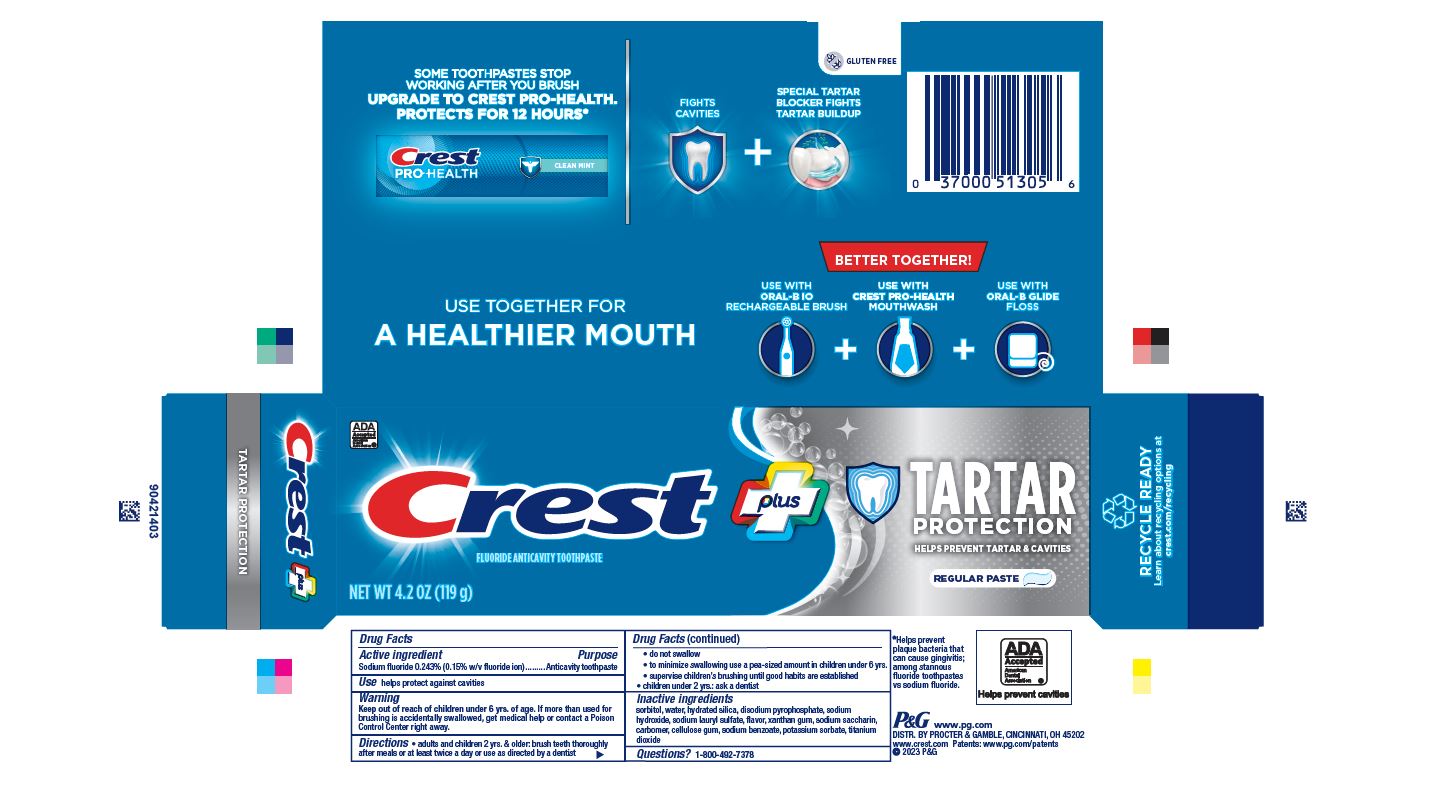 DRUG LABEL: Crest Plus Tartar Protection
NDC: 69423-817 | Form: PASTE, DENTIFRICE
Manufacturer: The Procter & Gamble Manufacturing Company
Category: otc | Type: HUMAN OTC DRUG LABEL
Date: 20260203

ACTIVE INGREDIENTS: SODIUM FLUORIDE 1.5 mg/1 g
INACTIVE INGREDIENTS: SODIUM BENZOATE; SODIUM ACID PYROPHOSPHATE; SODIUM HYDROXIDE; SODIUM LAURYL SULFATE; XANTHAN GUM; SACCHARIN SODIUM; CARBOXYMETHYLCELLULOSE SODIUM, UNSPECIFIED FORM; TITANIUM DIOXIDE; SORBITOL; WATER; HYDRATED SILICA; POTASSIUM SORBATE; CARBOXYPOLYMETHYLENE

Crest PlusTartar Protection

Drug Facts

Active ingredient

Sodium fluoride 0.243% (0.15% w/v fluoride ion)

Purpose

Anticavity toothpaste

Use

helps protect against cavities

Warning

Keep out of reach of children under 6 yrs. of age.If more than used for brushing is accidentally swallowed, get medical help or contact a Poison Control Center right away.

Directions

- adults and children 2 yrs. & older: brush teeth thoroughly after meals or at least twice a day or use as directed by a dentist
  - do not swallow
  - to minimize swallowing use a pea-sized amount in children under 6
  - supervise children's brushing until good habits are established
- children under 2 yrs.: ask a dentist

Inactive ingredients

sorbitol, water, hydrated silica, disodium pyrophosphate, sodium
hydroxide, sodium lauryl sulfate, flavor, xanthan gum, sodium saccharin,
carbomer, cellulose gum, sodium benzoate, potassium sorbate, titanium
dioxide

Questions?

1-800-492-7378

Dist. by Procter & Gamble, Cincinnati, OH 45202

PRINCIPAL DISPLAY PANEL - 161 g Tube Carton

ADA
Accepted
American
Dental
Association

Crest plus

FLUORIDE ANTICAVITY TOOTHPASTE
NET WT 4.2 OZ (119 g)

TARTAR
PROTECTION

HELPS PREVENT TARTAR & CAVITIES

Regular Paste